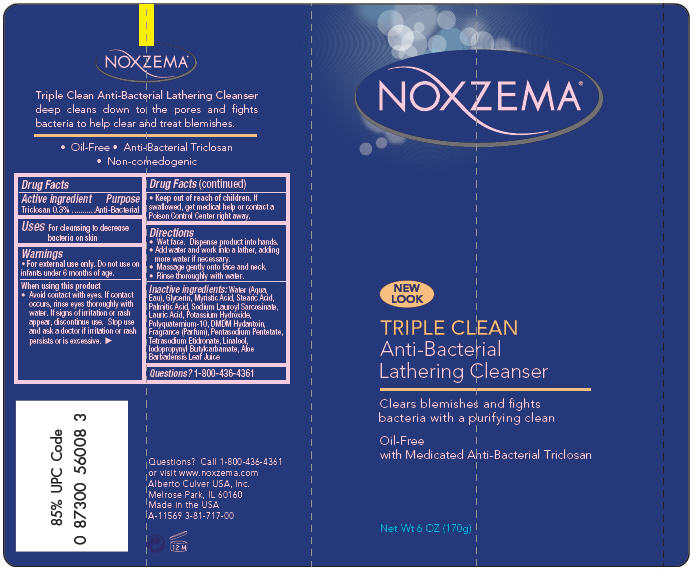 DRUG LABEL: Noxzema 
NDC: 12488-1000 | Form: SOAP
Manufacturer: Alberto-Culver USA Inc.
Category: otc | Type: HUMAN OTC DRUG LABEL
Date: 20091221

ACTIVE INGREDIENTS: Triclosan 0.003 g/1 g
INACTIVE INGREDIENTS: Water; Aloe Vera Leaf; Glycerin; Iodopropynyl Butylcarbamate; Palmitic Acid; Myristic Acid; Stearic Acid; Lauric Acid; Potassium Hydroxide

NOXZEMA®

Drug Facts

Active ingredient

Triclosan 0.3%

Purpose

Anti-Bacterial

Uses

For cleansing to decrease bacteria on skin

Warnings

DO NOT USE

- For external use only. Do not use on infants under 6 months of age.

When using this product

- Avoid contact with eyes. If contact occurs, rinse eyes thoroughly with water. If signs of irritation or rash appear, discontinue use. Stop use and ask a doctor if irritation or rash persists or is excessive.

Keep out of reach of children. If swallowed, get medical help or contact a Poison Control Center right away.

Directions

- Wet face. Dispense product into hands.
- Add water and work into a lather, adding more water if necessary.
- Massage gently onto face and neck.
- Rinse thoroughly with water.

Inactive ingredients

Water (Aqua, Eau), Glycerin, Myristic Acid, Stearic Acid, Palmitic Acid, Sodium Lauroyl Sarcosinate, Lauric Acid, Potassium Hydroxide, Polyquaternium-10, DMDM Hydantoin, Fragrance (Parfum), Pentasodium Pentetate, Tetrasodium Etidronate, Linalool, Iodopropynyl Butylcarbamate, Aloe Barbadensis Leaf Juice

Questions?

1-800-436-4361

Alberto Culver USA, Inc.
Melrose Park, IL 60160

PRINCIPAL DISPLAY PANEL - 6 oz Tube Label

NOXZEMA®

NEW
LOOK

TRIPLE CLEAN
Anti-Bacterial
Lathering Cleanser

Clears blemishes and fights
bacteria with a purifying clean

Oil-Free
with Medicated Anti-Bacterial Triclosan

Net Wt 6 OZ (170g)